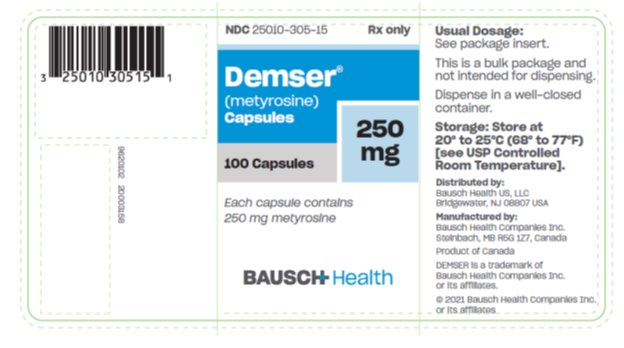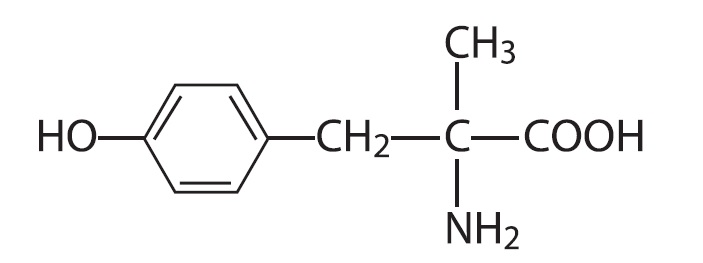 DRUG LABEL: Demser
NDC: 25010-305 | Form: CAPSULE
Manufacturer: Bausch Health US, LLC
Category: prescription | Type: HUMAN PRESCRIPTION DRUG LABEL
Date: 20210701

ACTIVE INGREDIENTS: metyrosine 250 mg/1 1
INACTIVE INGREDIENTS: silicon dioxide; FD&C Blue No. 2; magnesium stearate; titanium dioxide; GELATIN, UNSPECIFIED; HYDROXYPROPYL CELLULOSE, UNSPECIFIED

DEMSER®
(metyrosine)
Capsules

DESCRIPTION

DEMSER (metyrosine) is (–)-α-methyl-L-tyrosine or (α-MPT). It has the following structural formula:

Metyrosine is a white to off-white, crystalline compound of molecular weight 195.22. It is very slightly soluble in water, acetone, and methanol, and insoluble in chloroform and benzene. It is soluble in acidic aqueous solutions. It is also soluble in alkaline aqueous solutions, but is subject to oxidative degradation under these conditions.

DEMSER is supplied as capsules for oral administration. Each capsule contains 250 mg metyrosine.

Inactive ingredients are colloidal silicon dioxide, gelatin, hydroxypropyl cellulose, magnesium stearate, titanium dioxide, FD&C Blue 2 and edible black ink.

CLINICAL PHARMACOLOGY

DEMSER inhibits tyrosine hydroxylase, which catalyzes the first transformation in catecholamine biosynthesis, i.e., the conversion of tyrosine to dihydroxyphenylalanine (DOPA). Because the first step is also the rate-limiting step, blockade of tyrosine hydroxylase activity results in decreased endogenous levels of catecholamines, usually measured as decreased urinary excretion of catecholamines and their metabolites.

In patients with pheochromocytoma, who produce excessive amounts of norepinephrine and epinephrine, administration of 1 to 4 grams of DEMSER per day has reduced catecholamine biosynthesis from about 35% to 80% as measured by the total excretion of catecholamines and their metabolites (metanephrine and vanillylmandelic acid). The maximum biochemical effect usually occurs within two to three days, and the urinary concentration of catecholamines and their metabolites usually returns to pretreatment levels within three to four days after DEMSER is discontinued. In some patients the total excretion of catecholamines and catecholamine metabolites may be lowered to normal or near normal levels (less than 10 mg/24 hours). In most patients, the duration of treatment has been two to eight weeks, but several patients have received DEMSER for periods of 1 to 10 years.

Most patients with pheochromocytoma treated with DEMSER experience decreased frequency and severity of hypertensive attacks with their associated headache, nausea, sweating, and tachycardia. In patients who respond, blood pressure decreases progressively during the first two days of therapy with DEMSER; after withdrawal, blood pressure usually increases gradually to pretreatment values within two to three days.

Metyrosine is well absorbed from the gastrointestinal tract. From 53% to 88% (mean 69%) was recovered in the urine as unchanged drug following maintenance oral doses of 600 to 4000 mg/24 hours in patients with pheochromocytoma or essential hypertension. Less than 1% of the dose was recovered as catechol metabolites. These metabolites are probably not present in sufficient amounts to contribute to the biochemical effects of metyrosine. The quantities excreted, however, are sufficient to interfere with accurate determination of urinary catecholamines determined by routine techniques.

Plasma half-life of metyrosine determined over an 8-hour period after single oral doses was 3-3.7 hours in three patients.

For further information, refer to: Sjoerdsma A, Engelman K, Waldman TA, Cooperman LH, Hammond WG. Pheochromocytoma: Current Concepts of Diagnosis and Treatment: Combined Clinical Staff Conference at the National Institutes of Health. Ann Intern Med. 1966;65:1302-1326.

INDICATIONS AND USAGE

DEMSER is indicated in the treatment of patients with pheochromocytoma for:

1. Preoperative preparation of patients for surgery

2. Management of patients when surgery is contraindicated

3. Chronic treatment of patients with malignant pheochromocytoma

DEMSER is not recommended for the control of essential hypertension.

CONTRAINDICATIONS

DEMSER is contraindicated in persons known to be hypersensitive to this compound.

WARNINGS

Maintain Fluid Volume During and After Surgery
When DEMSER is used preoperatively, alone or especially in combination with alpha-adrenergic blocking drugs, adequate intravascular volume must be maintained intraoperatively (especially after tumor removal) and postoperatively to avoid hypotension and decreased perfusion of vital organs resulting from vasodilatation and expanded volume capacity. Following tumor removal, large volumes of plasma may be needed to maintain blood pressure and central venous pressure within the normal range.

In addition, life-threatening arrhythmias may occur during anesthesia and surgery, and may require treatment with a beta-blocker or lidocaine. During surgery, patients should have continuous monitoring of blood pressure and electrocardiogram.

Intraoperative Effects
While the preoperative use of DEMSER in patients with pheochromocytoma is thought to decrease intraoperative problems with blood pressure control, DEMSER does not eliminate the danger of hypertensive crises or arrhythmias during manipulation of the tumor, and the alpha-adrenergic blocking drug, phentolamine, may be needed.

Interaction with Alcohol
DEMSER may add to the sedative effects of alcohol and other CNS depressants, e.g., hypnotics, sedatives, and tranquilizers. (See PRECAUTIONS, Information for Patients and Drug Interactions.)

PRECAUTIONS

General

Information for Patients

When receiving DEMSER, patients should be warned about engaging in activities requiring mental alertness and motor coordination, such as driving a motor vehicle or operating machinery. DEMSER may have additive sedative effects with alcohol and other CNS depressants, e.g., hypnotics, sedatives, and tranquilizers.

Patients should be advised to maintain a liberal fluid intake. (See PRECAUTIONS, General.)

Drug Interactions

Caution should be observed in administering DEMSER to patients receiving phenothiazines or haloperidol because the extrapyramidal effects of these drugs can be expected to be potentiated by inhibition of catecholamine synthesis.

Concurrent use of DEMSER with alcohol or other CNS depressants can increase their sedative effects. (See WARNINGS and PRECAUTIONS,Information for Patients.)

Laboratory Test Interference

Spurious increases in urinary catecholamines may be observed in patients receiving DEMSER due to the presence of metabolites of the drug.

Carcinogenesis, Mutagenesis, Impairment of Fertility

Long-term carcinogenic studies in animals and studies on mutagenesis and impairment of fertility have not been performed with metyrosine.

Nursing Mothers

It is not known whether DEMSER is excreted in human milk. Because many drugs are excreted in human milk, caution should be exercised when DEMSER is administered to a nursing woman.

Pediatric Use

Safety and effectiveness in pediatric patients below the age of 12 years have not been established.

Geriatric Use

Clinical studies of DEMSER did not include sufficient numbers of subjects aged 65 and over to determine whether they respond differently from younger subjects. Other reported clinical experience has not identified differences in responses between the elderly and younger patients. In general, dose selection for an elderly patient should be cautious, usually starting at the low end of the dosing range, reflecting the greater frequency of decreased hepatic, renal, or cardiac function, and of concomitant disease or other drug therapy.

ADVERSE REACTIONS

Central Nervous System

Sedation usually is not obvious after one week unless the dosage is increased, but at dosages greater than 2000 mg/day some degree of sedation or fatigue may persist.

In most patients who experience sedation, temporary changes in sleep pattern occur following withdrawal of the drug. Changes consist of insomnia that may last for two or three days and feelings of increased alertness and ambition. Even patients who do not experience sedation while on DEMSER may report symptoms of psychic stimulation when the drug is discontinued.

Diarrhea

Diarrhea occurs in about 10% of patients and may be severe. Anti-diarrheal agents may be required if continuation of DEMSER is necessary.

Miscellaneous

Infrequently, slight swelling of the breast, galactorrhea, nasal stuffiness, decreased salivation, dry mouth, headache, nausea, vomiting, abdominal pain, and impotence or failure of ejaculation may occur. Crystalluria (see PRECAUTIONS) and transient dysuria and hematuria have been observed in a few patients. Hematologic disorders (including eosinophilia, anemia, thrombocytopenia, and thrombocytosis), increased SGOT levels, peripheral edema, and hypersensitivity reactions such as urticaria and pharyngeal edema have been reported rarely.

To report SUSPECTED ADVERSE REACTIONS, contact Bausch Health US, LLC at 1-800-321-4576 or FDA at 1-800-FDA-1088 or www.fda.gov/medwatch.

OVERDOSAGE

Signs of metyrosine overdosage include those central nervous system effects observed in some patients even at low dosages.

At doses exceeding 2000 mg/day, some degree of sedation or feeling of fatigue may persist. Doses of 2000-4000 mg/day can result in anxiety or agitated depression, neuromuscular effects (including fine tremor of the hands, gross tremor of the trunk, tightening of the jaw with trismus), diarrhea, and decreased salivation with dry mouth.

Reduction of drug dose or cessation of treatment results in the disappearance of these symptoms.

The acute toxicity of metyrosine was 442 mg/kg and 752 mg/kg in the female mouse and rat, respectively.

DOSAGE AND ADMINISTRATION

The recommended initial dosage of DEMSER for adults and children 12 years of age and older is 250 mg orally four times daily. This may be increased by 250 mg to 500 mg every day to a maximum of 4 g/day in divided doses. When used for preoperative preparation, the optimally effective dosage of DEMSER should be given for at least five to seven days.

Optimally effective dosages of DEMSER usually are between 2 and 3 g/day, and the dose should be titrated by monitoring clinical symptoms and catecholamine excretion. In patients who are hypertensive, dosage should be titrated to achieve normalization of blood pressure and control of clinical symptoms. In patients who are usually normotensive, dosage should be titrated to the amount that will reduce urinary metanephrines and/or vanillylmandelic acid by 50% or more.

If patients are not adequately controlled by the use of DEMSER, an alpha-adrenergic blocking agent (phenoxybenzamine) should be added.

Use of DEMSER in children under 12 years of age has been limited and a dosage schedule for this age group cannot be given.

HOW SUPPLIED

DEMSER Capsules 250 mg are blue opaque capsules imprinted with “ATON/305” on body, and “DEMSER” on cap, filled with white to off-white granular free-flowing powder. They are supplied as follows:

NDC 25010-305-15 bottles of 100

Storage: Store at 20° to 25°C (68° to 77°F) [see USP Controlled Room Temperature].

Dispense in a well-closed container.

Distributed by:

Bausch Health US, LLC

Bridgewater, NJ 08807 USA

Manufactured by:

Bausch Health Companies Inc.

Steinbach, MB R5G 1Z7, Canada

DEMSER is a trademark of Bausch Health Companies Inc. or its affiliates.

© 2021 Bausch Health Companies Inc. or its affiliates

Rev. 07/2021 9620202 20003159

Package/Label Display Panel - 250 mg Capsules Label

NDC 25010-305-15

Rx only

Demser®
(metyrosine)
Capsules

250 mg

100 Capsules

Each capsule contains
250 mg metyrosine

BAUSCH Health